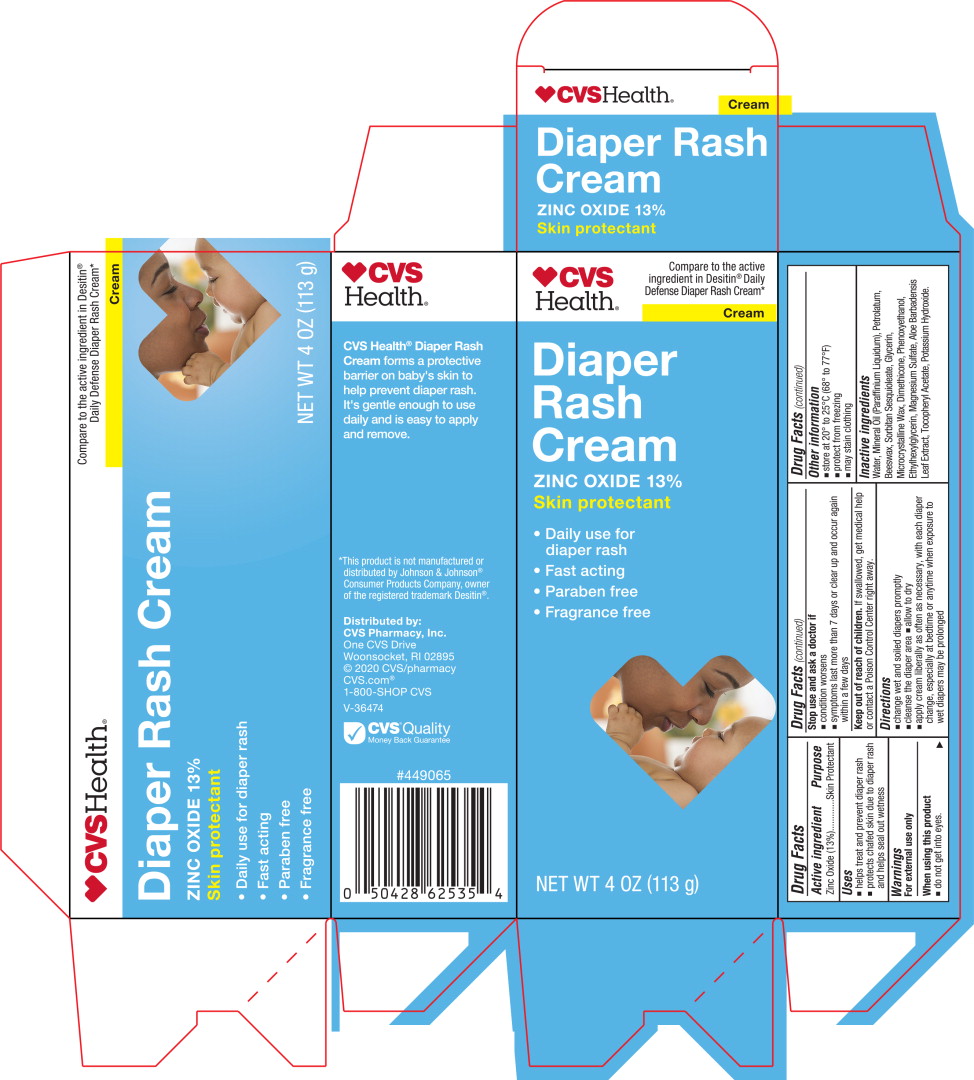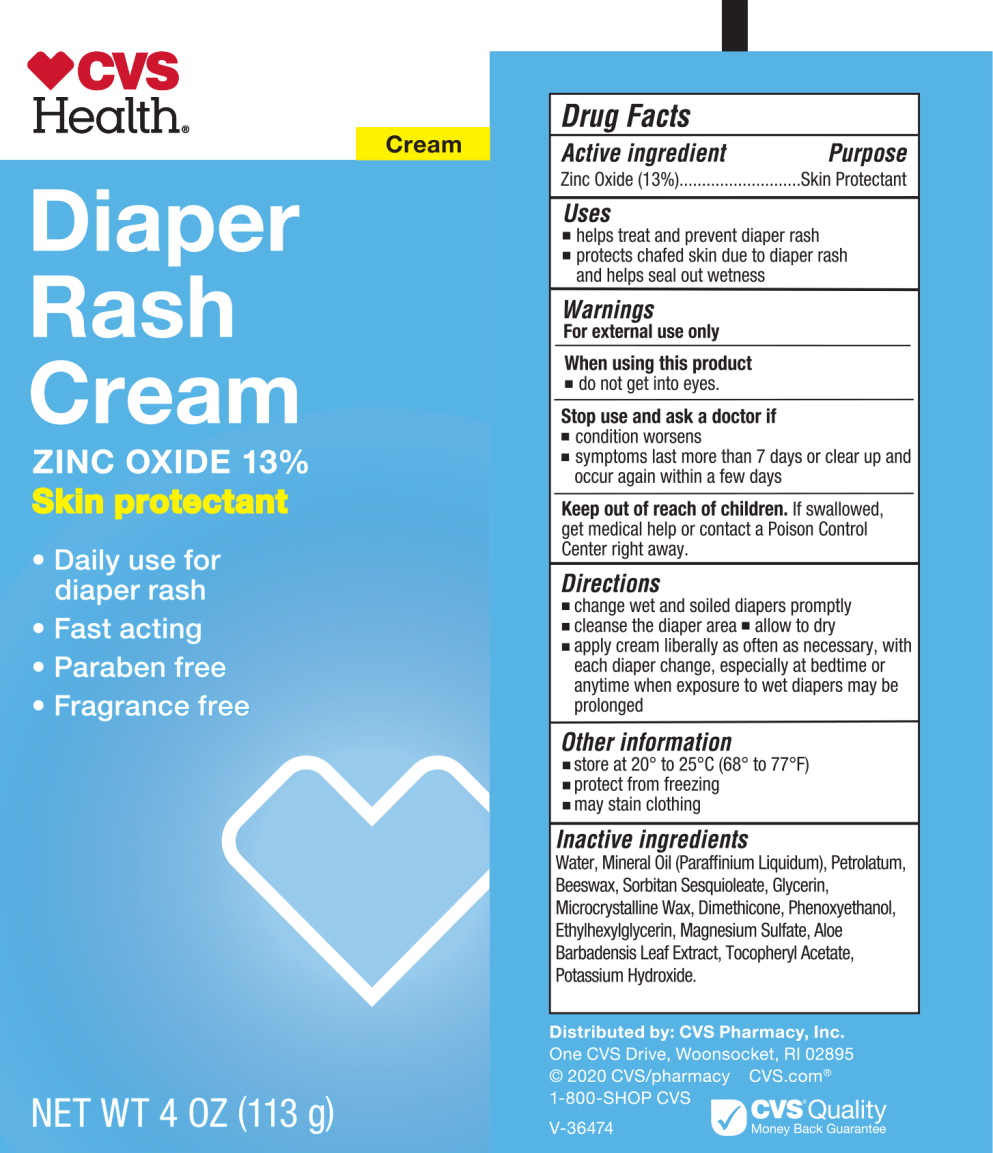 DRUG LABEL: CVS Health Diaper Rash
NDC: 66902-449 | Form: CREAM
Manufacturer: NATURAL ESSENTIALS, INC.
Category: otc | Type: HUMAN OTC DRUG LABEL
Date: 20241001

ACTIVE INGREDIENTS: ZINC OXIDE 14.7 g/113 g
INACTIVE INGREDIENTS: WATER; MINERAL OIL; PETROLATUM; WHITE WAX; SORBITAN SESQUIOLEATE; GLYCERIN; MICROCRYSTALLINE WAX; DIMETHICONE; PHENOXYETHANOL; ETHYLHEXYLGLYCERIN; MAGNESIUM SULFATE, UNSPECIFIED FORM; ALOE VERA LEAF; .ALPHA.-TOCOPHEROL; POTASSIUM HYDROXIDE

Drug Facts

Active ingredient

Zinc Oxide (13%)

Purpose

Skin Protectant

Uses

- helps treat and prevent diaper rash
- protects chafed skin due to diaper rash and helps seal out wetness

Warnings

For external use only

When using this product

- do not get into eyes.

Stop use and ask a doctor if

- condition worsens
- symptoms last more than 7 days or clear up and occur again within a few days

Keep out of reach of children.

If swallowed, get medical help or contact a Poison Control Center right away.

Directions

- change wet and soiled diapers promptly
- cleanse the diaper area
- allow to dry
- apply cream liberally as often as necessary, with each diaper change, especially at bedtime or anytime when exposure to wet diapers may be prolonged

Other information

- store at 20° to 25°C (68° to 77°F)
- protect from freezing
- may stain clothing

Inactive ingredients

Water, Mineral Oil (Paraffinium Liquidum), Petrolatum, Beeswax, Sorbitan Sesquioleate, Glycerin, Microcrystalline Wax, Dimethicone, Phenoxyethanol, Ethylhexylglycerin, Magnesium Sulfate, Aloe Barbadensis Leaf Extract, Tocopheryl Acetate, Potassium Hydroxide.

Principal Display Panel – Box Label

CVS

Health®

Compare to the active
ingredient in Desitin®Daily
Defense Diaper Rash Cream*

Cream

Diaper
Rash
Cream

ZINC OXIDE 13%

Skin protectant

Daily use for
diaper rash

Fast acting

Paraben Free

Fragrance free

NET WT 4 OZ (113 g)

Principal Display Panel – Tube Label

CVS

Health®

Cream

Diaper
Rash
Cream

ZINC OXIDE 13%

Skin protectant

Daily use for
diaper rash

Fast acting

Paraben Free

Fragrance free

NET WT 4 OZ (113 g)